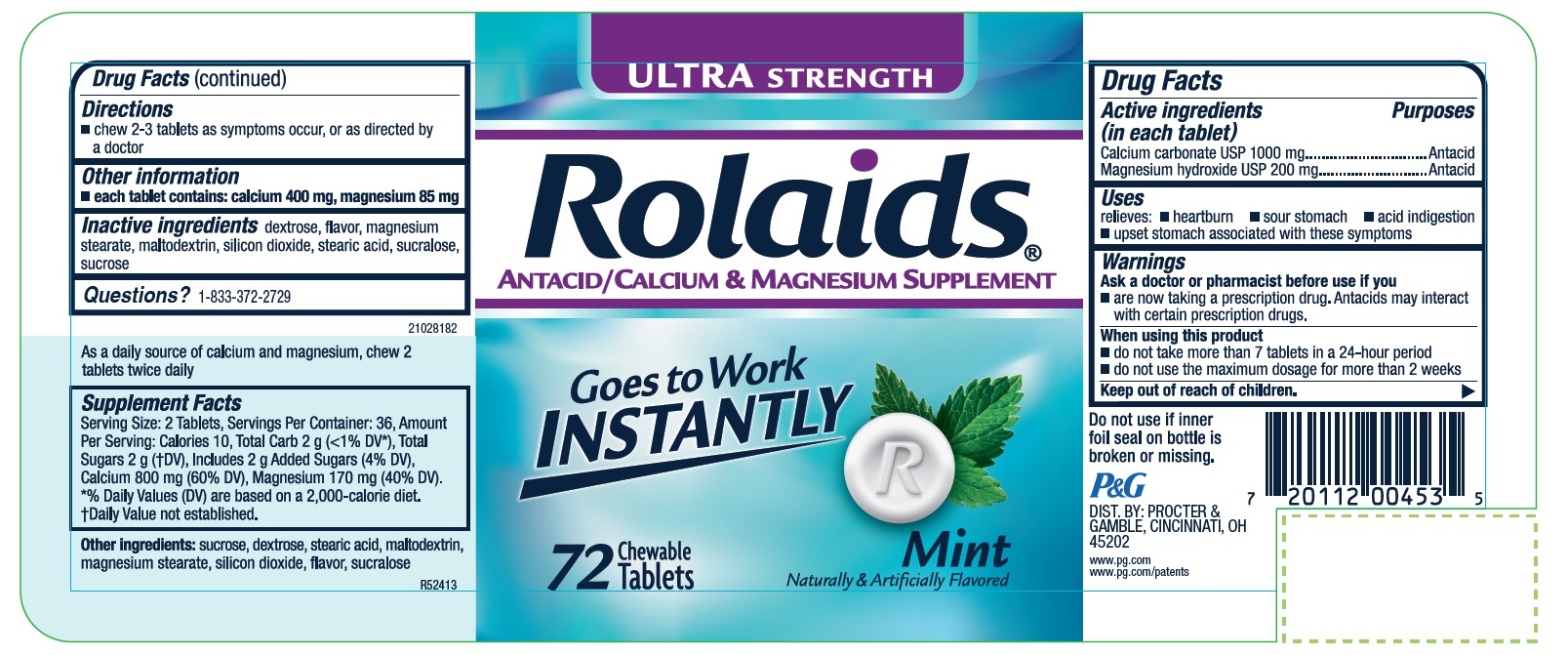 DRUG LABEL: Rolaids Ultra Strength
NDC: 69423-828 | Form: TABLET, CHEWABLE
Manufacturer: THE PROCTER & GAMBLE MANUFACTURING COMPANY
Category: otc | Type: HUMAN OTC DRUG LABEL
Date: 20251003

ACTIVE INGREDIENTS: CALCIUM CARBONATE 1000 mg/1 1; MAGNESIUM HYDROXIDE 200 mg/1 1
INACTIVE INGREDIENTS: DEXTROSE; MAGNESIUM STEARATE; SILICON DIOXIDE; STEARIC ACID; SUCRALOSE; SUCROSE; MALTODEXTRIN

Rolaids Ultra Strength Tablets Mint

ULTRASTRENGTHRolaids Mint 72 Chewable Tablets

Drug Facts

Active ingredients

(in each tablet)
Calcium carbonate USP 1000 mg
Magnesium hydroxide USP 200 mg

Purposes

Antacid

Antacid

Uses

relieves:

- heartburn
- sour stomach
- acid indigestion
- upset stomach associated with these symptoms

Warnings

Ask a doctor or pharmacist before use if you

- are now taking a prescription drug. Antacids may interact with certain prescription drugs.

When using this product

- do not take more than 7 tablets in a 24-hour period
- do not use the maximum dosage for more than 2 weeks

Directions

- chew 2-3 tablets as symptoms occur, or as directed by a doctor

Other information

each tablet contains: calcium 400 mg, magnesium 85 mg

Inactive ingredients

dextrose, flavor, magnesium stearate, maltodextrin, silicon dioxide, stearic acid, sucralose, sucrose

Questions?

1-833-372-2729

Tamper Evident

Do not use if inner foil seal on bottle is broken or missing

DIST. BY: PROCTER & GAMBLE, CINCINNATI, OH 45202

PRINCIPAL DISPLAY PANEL

ULTRASTRENGTH
Rolaids®
ANTACID/CALCIUM & MAGNESIUM SUPPLEMENT
Goes to Work Instantly
Mint

Naturally and Artificially flavored

72 Chewable Tablets